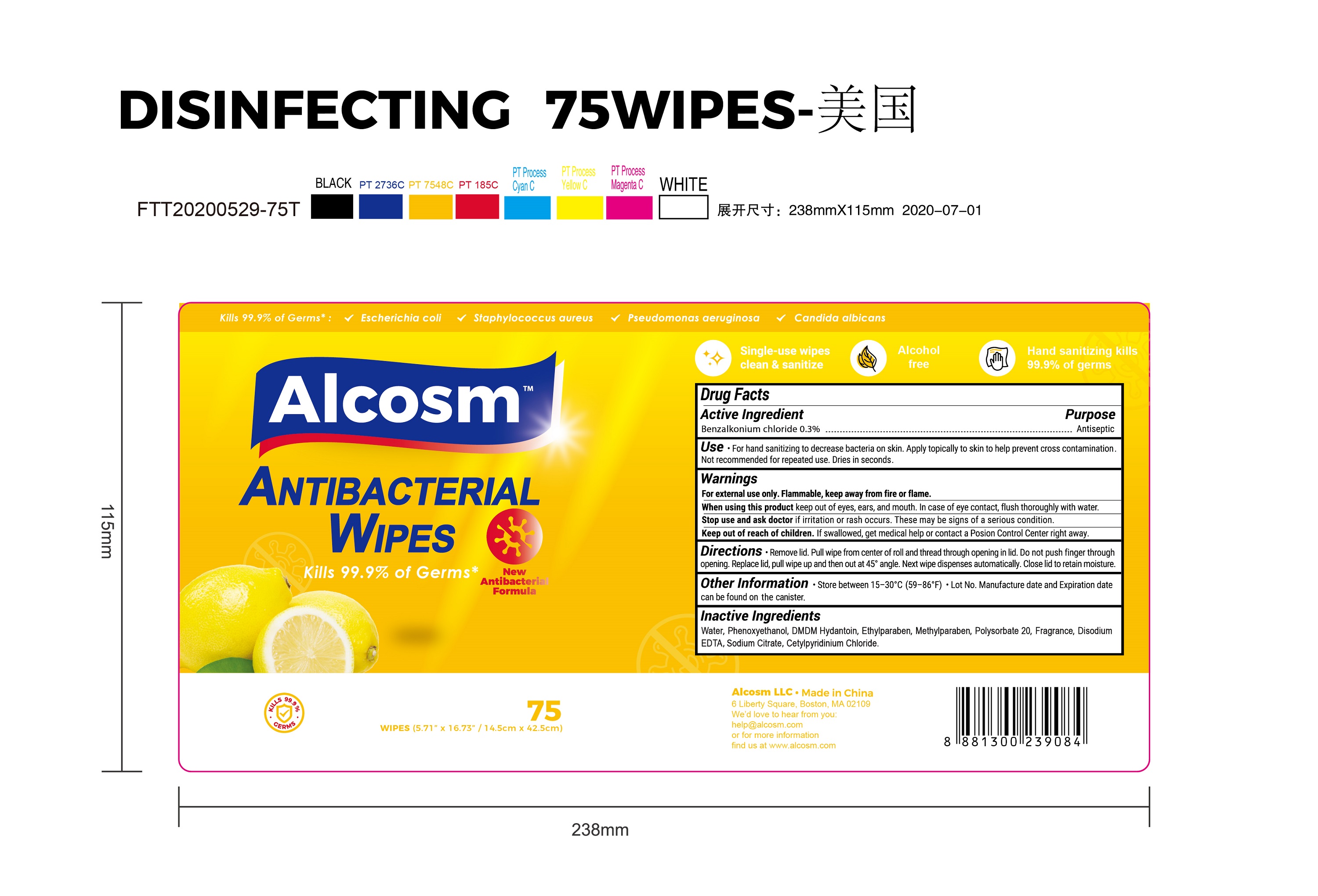 DRUG LABEL: Alcosm Antibacterial wipes
NDC: 75109-507 | Form: CLOTH
Manufacturer: Kangna (Zhejiang) Medical Supplies Co., Ltd.
Category: otc | Type: HUMAN OTC DRUG LABEL
Date: 20220114

ACTIVE INGREDIENTS: BENZALKONIUM CHLORIDE 0.3 g/100 g
INACTIVE INGREDIENTS: CETYLPYRIDINIUM CHLORIDE; WATER; DMDM HYDANTOIN; POLYSORBATE 20; PHENOXYETHANOL; ETHYLPARABEN; EDETATE DISODIUM ANHYDROUS; METHYLPARABEN; SODIUM CITRATE

75109-507 Alcosm Antibacterial Wipes 0.3% Benzalkonium Chloride

Active Ingredient

Benzalkonium Chloride 0.3%

Purpose

Antiseptic

USE

●For hand sanitizing to decrease bacteria on the skin.
●Apply topically to the skin to help prevent cross contamination.
●Not recommended for repeated use.
●Dries in seconds.

Warning

For external use only. Flammable, keep away from fire or flame.
When using this product keep out of eyes, ears, and mouth. In case of eye contact, flush thoroughly with water.
Stop use and ask doctor if irritation or rash occurs. These may be signs of a serious condition.

Keep out of reach of children. If swallowed, get medical help or contact a Posion Control Center right away.

Directions

Remove lid. Pull wipe from center of roll and thread through opening in lid. Do not push finger through
opening. Replace lid, pull wipe up and then out at 45° angle. Next wipe dispenses automatically. Close lid to retain moisture.

Inactive ingredients

Water, Phenoxyethanol, DMDM Hydantoin, Ethylparaben, Methylparaben, Polysorbate 20, Fragrance, Disodium
EDTA, Sodium Citrate, Cetylpyridinium Chloride.